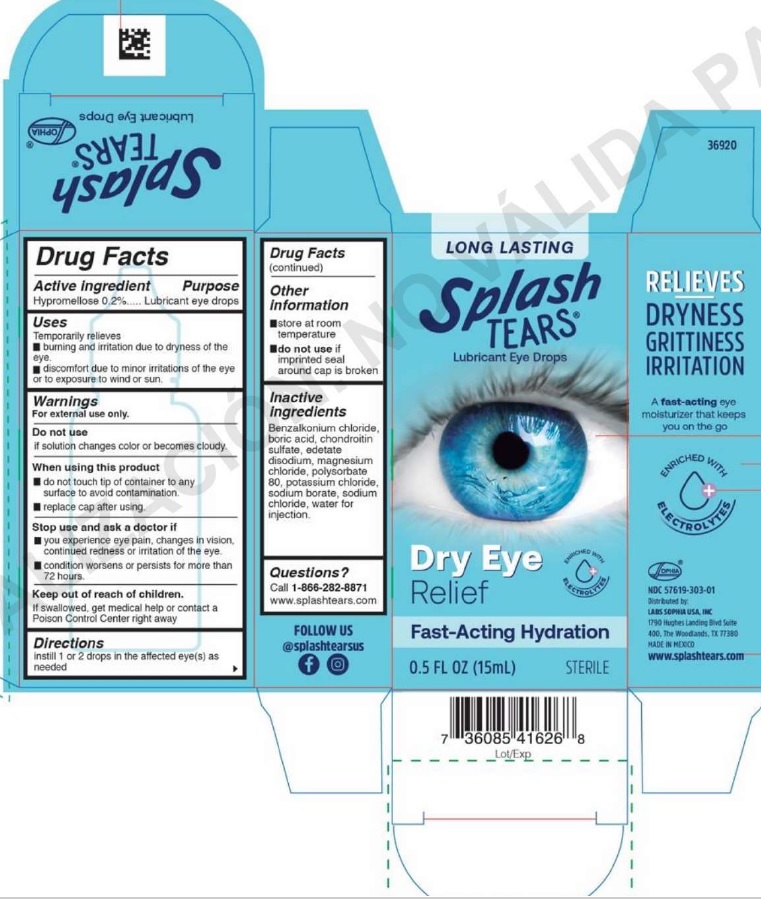 DRUG LABEL: Splash Tears
NDC: 57619-303 | Form: SOLUTION/ DROPS
Manufacturer: LABORATORIOS SOPHIA, S.A. DE C.V.
Category: otc | Type: HUMAN OTC DRUG LABEL
Date: 20250509

ACTIVE INGREDIENTS: HYPROMELLOSE 2910 (4000 MPA.S) 0.2 g/100 mL
INACTIVE INGREDIENTS: BENZALKONIUM CHLORIDE; CHONDROITIN SULFATE (BOVINE); EDETATE DISODIUM; POLYSORBATE 80; WATER; MAGNESIUM CHLORIDE; SODIUM BORATE; SODIUM CHLORIDE; POTASSIUM CHLORIDE; BORIC ACID

Splash Tears

Drug Facts

Active ingredient

Hypromellose 0.2%

Purpose

Lubricant eye drops

Uses

Temporarily relieves

- burning and irritation due to dryness of the eye.
- discomfort due to minor irritations of the eye or to exposure to wind or sun.

Warnings

For external use only.

Do not use if solution changes color or becomes cloudy.

When using this product

- do not touch tip of container to any surface to avoid contamination.
- replace cap after using.

Stop use and ask a doctor if

- you experience eye pain, changes in vision, continued redness or irritation of the eye.
- condition worsens or persists for more than 72 hours.

Keep out of reach of children. If swallowed, get medical help or contact a Poison Control Center right away.

Directions

instill 1 or 2 drops in the affected eye(s) as needed

Other information

- store at room temperature
- do not use if imprinted seal around cap is broken.

Inactive ingredients

benzalkonium chloride, boric acid, chondroitin sulfate, edetate disodium, magnesium chloride, polysorbate 80, potassium chloride, sodium borate, sodium chloride, water for injection

Questions?

Call 1-866-282-8871

www.splashtears.com

NDC 57619-303-01

Distributed by:

LABS SOPHIA USA, INC.

1790 Hughes Landing Blvd Suite 400

The Woodlands, TX 77380

MADE IN MEXICO

www.splashtears.com

PACKAGE LABEL

LONG LASTING

Splash TEARS®

Lubricant Eye Drops

Dry Eye Relief

Fast-Acting Hydration

0.5 FL OZ (15 mL)

STERILE